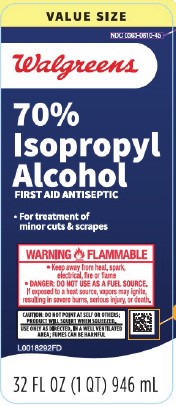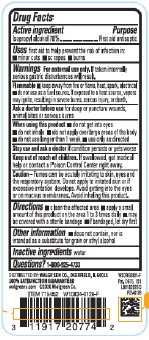 DRUG LABEL: 70%
NDC: 0363-0810 | Form: LIQUID
Manufacturer: Walgreen Co.
Category: otc | Type: HUMAN OTC DRUG LABEL
Date: 20260210

ACTIVE INGREDIENTS: ISOPROPYL ALCOHOL 70 mL/100 mL
INACTIVE INGREDIENTS: WATER

Walgreens 810.003/810AA
70% Isopropyl Alcohol

Active ingredient

Isopropyl alcohol 70%

Purpose

First aid antiseptic

Uses

first aid to help prevent the risk of infection in:

- minor cuts
- scrapes
- burns

Warnings

For external use only. If taken internally serious gastric disturbances will result.

Flammable

- keep away from fire or flame, heat, spark, electrical
- do not use as a fuel source. If exposed to a heat source, vapors may ignite, resulting in severe burns, serious injury, or death.

Ask a Doctor before use

for deep or puncture wounds, animal bites or serious burns

When using this product

- do not get into eyes
- do not inhale
- do not apply over large areas of the body
- do not use longer than 1 week
- use only as directed

Stop use and ask a doctor

If condition persists or gets worse

Keep out of reach of children.

If swallowed, get medical help or contact a Poison Control Center right away.

Caution

Fumes can be acutely irritating to skin, eyes and the respiratory system. Do not apply to irritated skin or if excessive irritation develops. Avoid getting into the eyes or mucous membranes. Avoid inhaling this product.

Directions

- clean the affected area
- apply a small amount of this product on the affected area 1 to 3 times daily
- may be covered with a sterile bandage
- if bandaged, let dry first

Other information

- does not contain, nor is intended as a substitute for grain or ethyl alcohol

Inactive ingredient

water

Questions?

1-800-925-4733

ADVERSE REACTION

DISTRIBUTED BY: WALGREEN CO., DEERFIELD, IL 60015

100% SATISFACTION GUARANTEED walgreens.com ©2026 Walgreen Co.

Pat. D675, 101

Principal display panel

VALUE SIZE

NDC 0363-0810-45

Walgreens

70% Isopropyl Alcohol

First Aid Antiseptic

- For treatment of minor cuts & scrapes

WARNING FLAMMABLE

- Keep away from heat, spark, electrical, fire or flame
- DANGER: DO NOT USE AS A FUEL SOURCE.

If exposed to a heat source, vapors may ignite, resulting in severe burns, serious injury, or death.

CAUTION: DO NOT POINT AT SELF OR OTHERS: PRODUCT WILL SQUIRT WHEN SQUEEZED.

USE ONLY AS DIRECTED, IN A WELL-VENTILATED AREA; FUMES MAY BE HARMFUL

32 FL OZ (1 QT) 946 mL